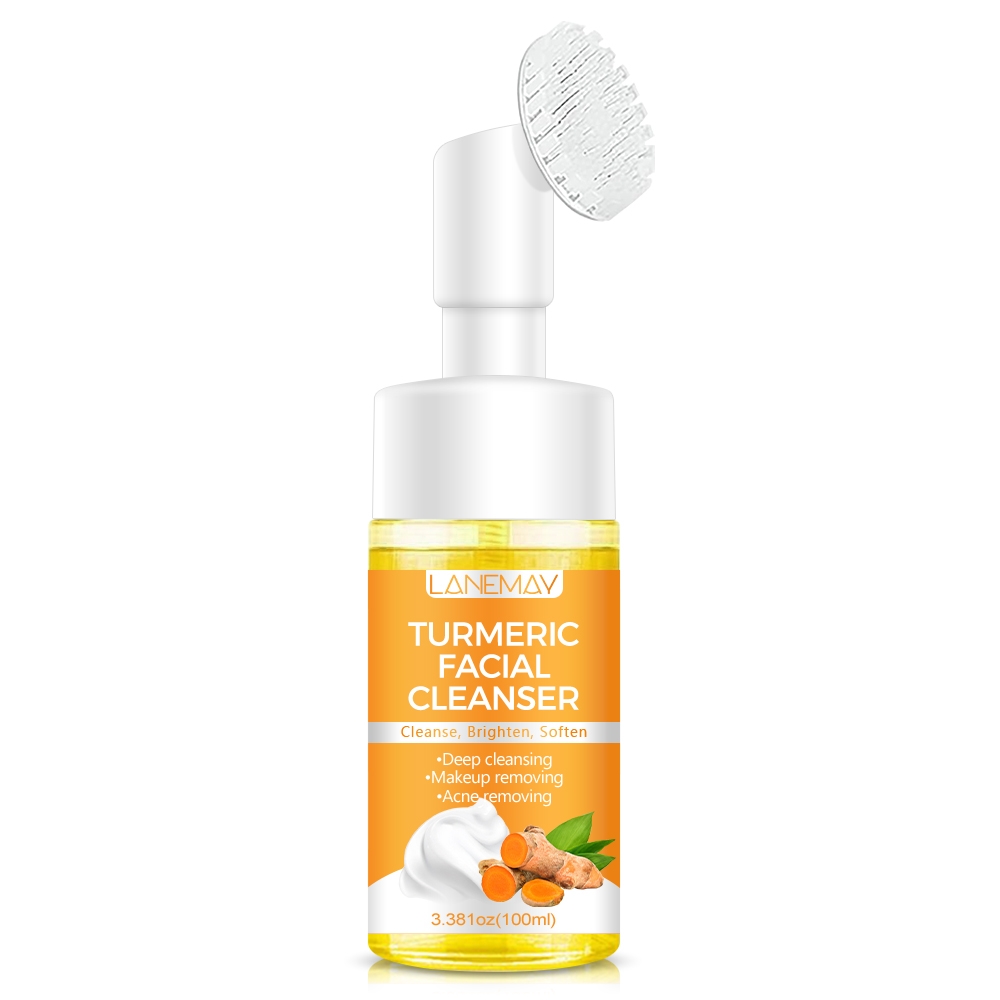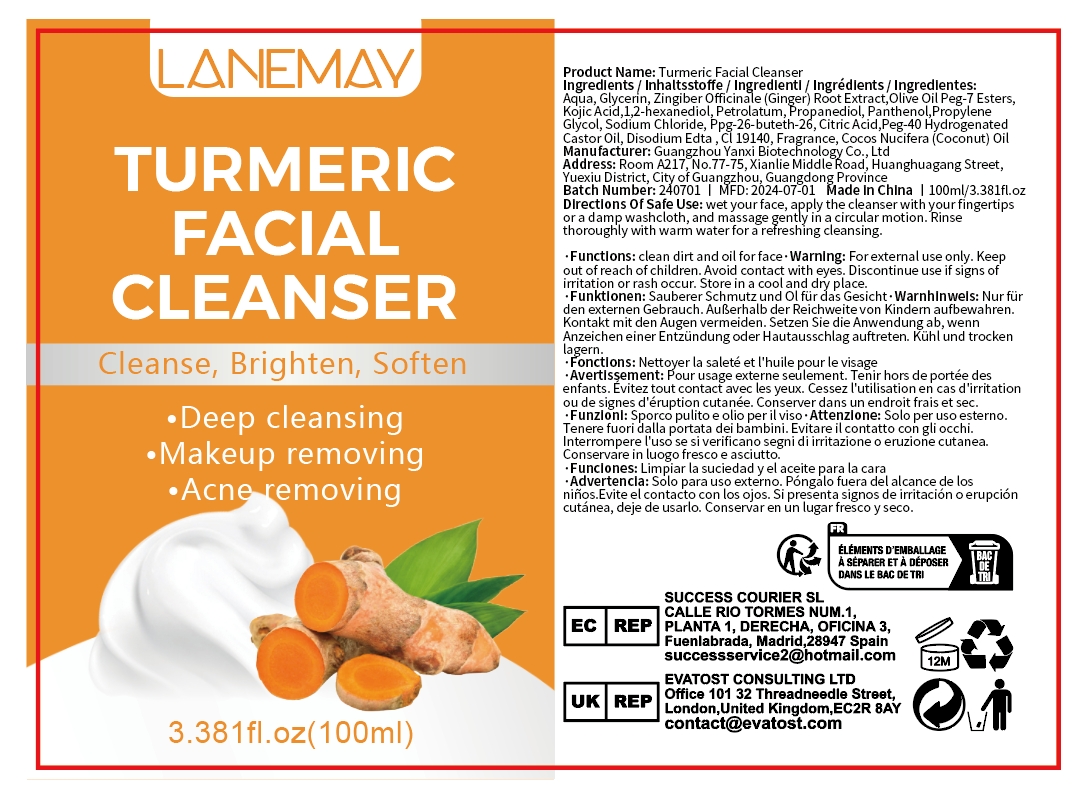 DRUG LABEL: Turmeric Facial cleanser
NDC: 84025-185 | Form: LIQUID
Manufacturer: Guangzhou Yanxi Biotechnology Co.. Ltd
Category: otc | Type: HUMAN OTC DRUG LABEL
Date: 20240909

ACTIVE INGREDIENTS: GLYCERIN 5 mg/100 mL; KOJIC ACID 3 mg/100 mL
INACTIVE INGREDIENTS: WATER

DOSAGE AND ADMINISTRATION

Cream for cleansing the skin and removing facial acne

WARNINGS

keep out of children

INACTIVE INGREDIENT

AQUA

INDICATIONS AND USAGE

for daily skin care

keep out of children

PURPOSE

Effective for cleaning facial pores and after-makeup care